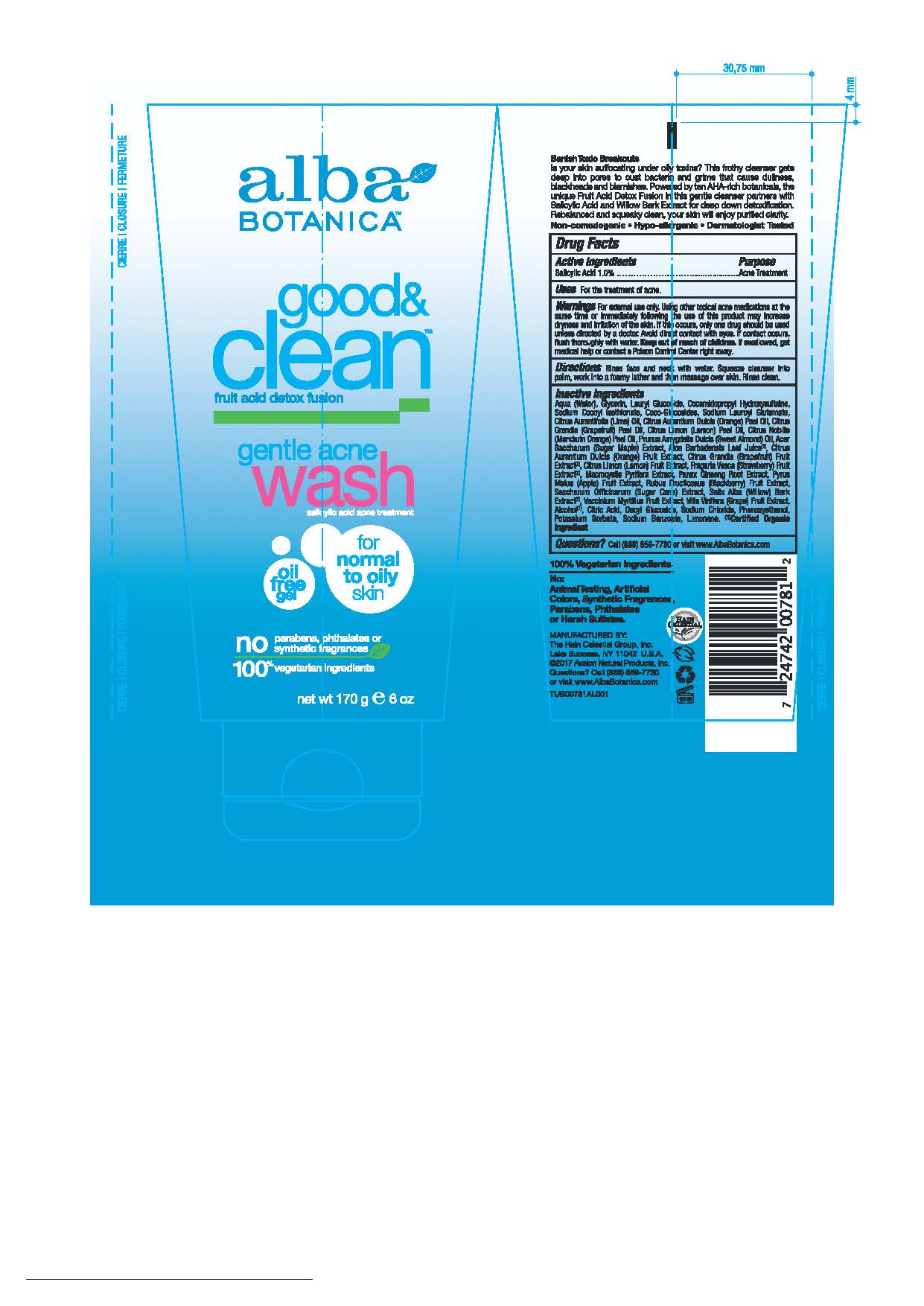 DRUG LABEL: AL0078101 Alba Botanica Good and Clean Acne Wash
NDC: 61995-2081 | Form: LOTION
Manufacturer: The Hain Celestial Group, Inc.
Category: otc | Type: HUMAN OTC DRUG LABEL
Date: 20210205

ACTIVE INGREDIENTS: SALICYLIC ACID 1 g/100 g
INACTIVE INGREDIENTS: ALPINE STRAWBERRY; MACROCYSTIS PYRIFERA; ASIAN GINSENG; APPLE; SALIX ALBA BARK; WINE GRAPE; LEMON; LAURYL GLUCOSIDE; WATER; GLYCERIN; COCO GLUCOSIDE; SODIUM LAUROYL GLUTAMATE; ACER SACCHARUM BARK/SAP; ALOE VERA LEAF; ORANGE; PUMMELO; BLACKBERRY; SUGARCANE; BILBERRY; CITRUS MAXIMA FRUIT RIND OIL; LIME OIL; ORANGE OIL; LEMON OIL; MANDARIN OIL; ALMOND OIL; CITRIC ACID MONOHYDRATE; DECYL GLUCOSIDE; GLYCERYL OLEATE; ALCOHOL; PHENOXYETHANOL; POTASSIUM SORBATE; SODIUM BENZOATE; SODIUM COCOYL ISETHIONATE; COCAMIDOPROPYL HYDROXYSULTAINE; SODIUM CHLORIDE

Alba Botanica Good & Clean Acne Wash

Active Ingredient

Salicylic Acid- 1.0%

DOSAGE AND ADMINISTRATION

Rinse face and neck with water. Squeze cleanser into palm, work into a foamy lather and then massage over the skin. Rinse clean.

PURPOSE

Acne Treatment

WARNINGS

For external use only. Using other topical acne medications at the same time or immediately following the use of this product may increase dryness and irritation of the skin. If this occurs, only one drug should be used unless directed by a doctor. Avoid direct contact with eyes. If contact occurs, flush throughly with water.

Keep out of reach of children. If swallowed get medical help or contact Poison Center right away.

INACTIVE INGREDIENT

Water, Glycerin, Lauryl Glucoside, Cocamidopropyl Hydroxysultaine, Sodium Cocoyl Isothionate, Coco-glucosides, Sodium Lauroyl Glutamate, Acer Saccharum (Sugar Maple) Extract, Aloe Barbadensis Leaf Juice(1), Citrus Aurantium Dulcis (Orange) Peel Extract, Citrus Grandis (Grapefruit) Fruit Extract (1), Citrus Limon (Lemon) Fruit Extract, Fragaria Vesca (Strawberry) Fruit Extract (1), Macrocystis Pyrifera Extract, Panax Ginseng Root Extract, Purys Malus (Apple) Extract, Rubus Fruticosus (Blackberry) Fruit Extract, Saccharum Officinarum (Sugar Cane) Extract, Salix Alba (Willow) Bark Extract (1), Vitis Vinifera(Grape) Fruit Extract, Vaccinium Myrtillus Fruit Extract, Citrus Aurantifolia (Lime) Oil (2), Citrus Aurantium Dulcis (Orange) Peel Oil (2), Citrus Grandis (Grapefruit) Peel Oil (2), Citrus Limon (Lemon) Peel Oil (2), Citrus Nobilis (Mandarin Orange) Peel Oil (2), Prunus Amygdalus Dulcis (Sweet Almond) Oil (2), Citric Acid, Decyl Glucoside, Alcohol (1), Sodium Chloride, Phenoxyethanol, Sodium Benzoate, Potassium Sorbate.

(1) Certified Organicf Ingredient; (2) For scent only

INDICATIONS AND USAGE

For the treatment of acne.